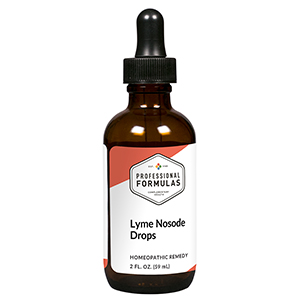 DRUG LABEL: Lyme Nosode Drops
NDC: 63083-2128 | Form: LIQUID
Manufacturer: Professional Complementary Health Formulas
Category: homeopathic | Type: HUMAN OTC DRUG LABEL
Date: 20190815

ACTIVE INGREDIENTS: ANGELICA ARCHANGELICA ROOT 2 [hp_X]/59 mL; ANGELICA PUBESCENS ROOT 2 [hp_X]/59 mL; GAMBIR 2 [hp_X]/59 mL; MAGNESIUM PHOSPHATE, DIBASIC TRIHYDRATE 2 [hp_X]/59 mL; POTASSIUM CHLORIDE 3 [hp_X]/59 mL; MANGANESE 3 [hp_X]/59 mL; YUCCA FILAMENTOSA WHOLE 3 [hp_X]/59 mL; BOVINE TYPE II COLLAGEN (TRACHEAL CARTILAGE) 3 [hp_X]/59 mL; PHYTOLACCA AMERICANA ROOT 4 [hp_X]/59 mL; GOLDENSEAL 5 [hp_X]/59 mL; TOXICODENDRON PUBESCENS LEAF 6 [hp_X]/59 mL; CAUSTICUM 6 [hp_X]/59 mL; LATIGLUTENASE 8 [hp_X]/59 mL; OXALIC ACID 8 [hp_X]/59 mL; ARNICA MONTANA WHOLE 8 [hp_X]/59 mL; LATRODECTUS MACTANS 10 [hp_X]/59 mL; BORRELIA BURGDORFERI 12 [hp_X]/59 mL; TREPONEMIC SKIN CANKER HUMAN 12 [hp_X]/59 mL; RICKETTSIA AKARI 12 [hp_X]/59 mL; BABESIA MICROTI 12 [hp_X]/59 mL; EHRLICHIA CHAFFEENSIS 12 [hp_X]/59 mL
INACTIVE INGREDIENTS: ALCOHOL; WATER

C128

ACTIVE INGREDIENTS

Angelica archangelica 2X
Du huo 2X
Shujin chin 2X
Magnesia phosphorica 2X, 3X, 6X
Kali muriaticum 3X
Manganum metallicum 3X
Yucca filamentosa 3X
Cartilage 3X, 6X, 12X
Phytolacca decandra 4X, 12X, 30X
Hydrastis canadensis 5X
Rhus toxicodendron 6X
Causticum 6X, 12X, 30X
Hordeum vulgare 8X
Oxalicum acidum 8X, 12X
Arnica montana 8X, 100X, 1000X
Latrodectus mactans 10X
Lyme nosode 12X, 30X, 60X
Syphilinum 12X, 30X, 60X
Lyme infested deer ticks 12X, 30X, 60X
Rocky mountain spotted fever 12X, 30X, 60X
Babesia microti 12X, 30X, 60X
Ehrlichia chaffeensis 12X, 30X, 60X

QUESTIONS

Professional Formulas

PO Box 2034 Lake Oswego, OR 97035

INDICATIONS

For the temporary relief of minor aches in the muscles or joints, chills, sweats, fatigue, or nausea.*

PURPOSE

*Claims based on traditional homeopathic practice, not accepted medical evidence. Not FDA evaluated.

WARNINGS

Persistent symptoms may be a sign of a serious condition. If symptoms persist or are accompanied by a fever, rash, or persistent headache, consult a doctor. Keep out of the reach of children. In case of overdose, get medical help or contact a poison control center right away. If pregnant or breastfeeding, ask a healthcare professional before use.

Keep out of the reach of children.

PREGNANCY OR BREAST FEEDING

If pregnant or breastfeeding, ask a healthcare professional before use.

DIRECTIONS

Place drops under tongue 30 minutes before/after meals. Adults and children 12 years and over: Take 10 to 15 drops once weekly or monthly. If mild symptoms are present, take 10 drops up to 3 times per day. Consult a physician for use in children under 12 years of age.

OTHER INFORMATION

Tamper resistant. If seal is broken, do not use. After opening, close container tightly and store at room temperature away from heat.

INACTIVE INGREDIENTS

20% ethanol, purified water.

LABEL

Est 1985

Professional Formulas

Complementary Health

Lyme Nosode Drops

Homeopathic Remedy

2 FL. OZ. (59 mL)